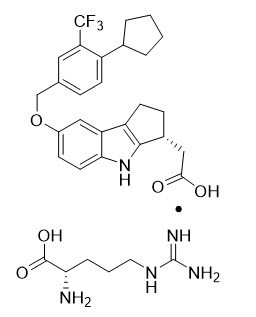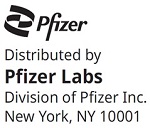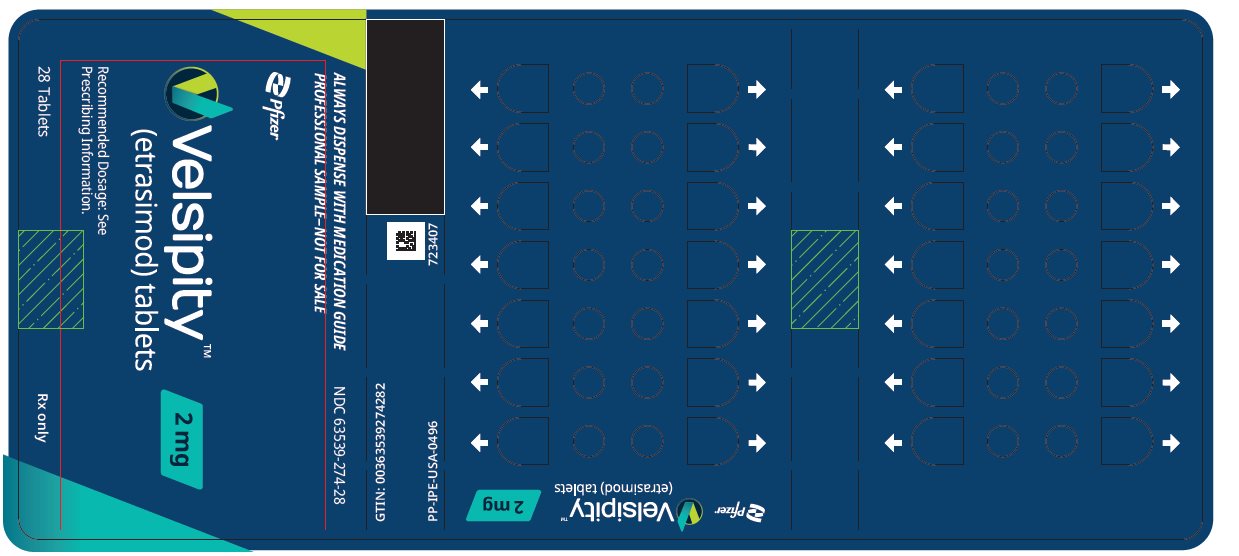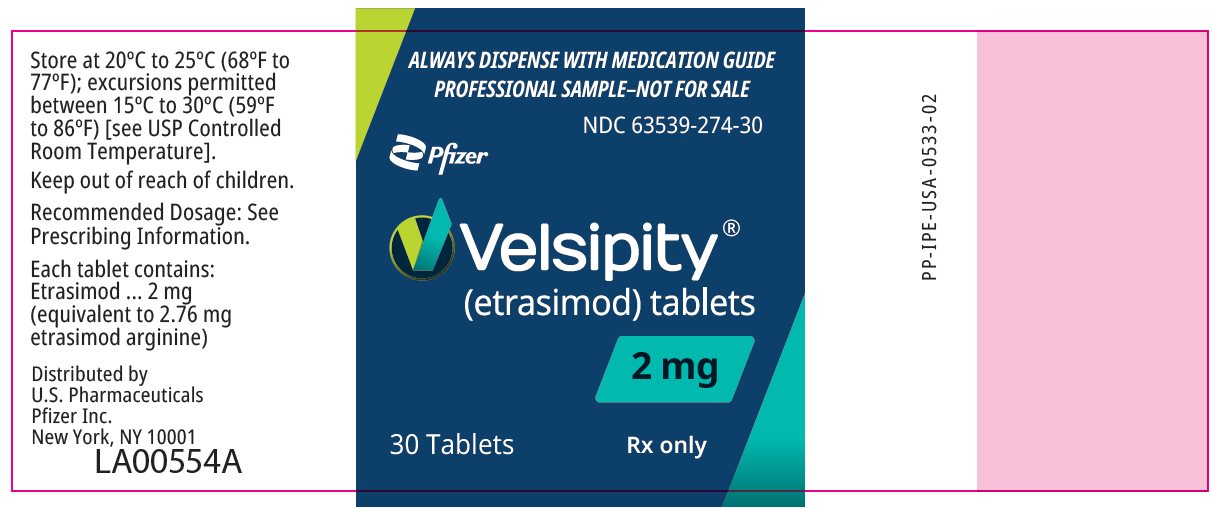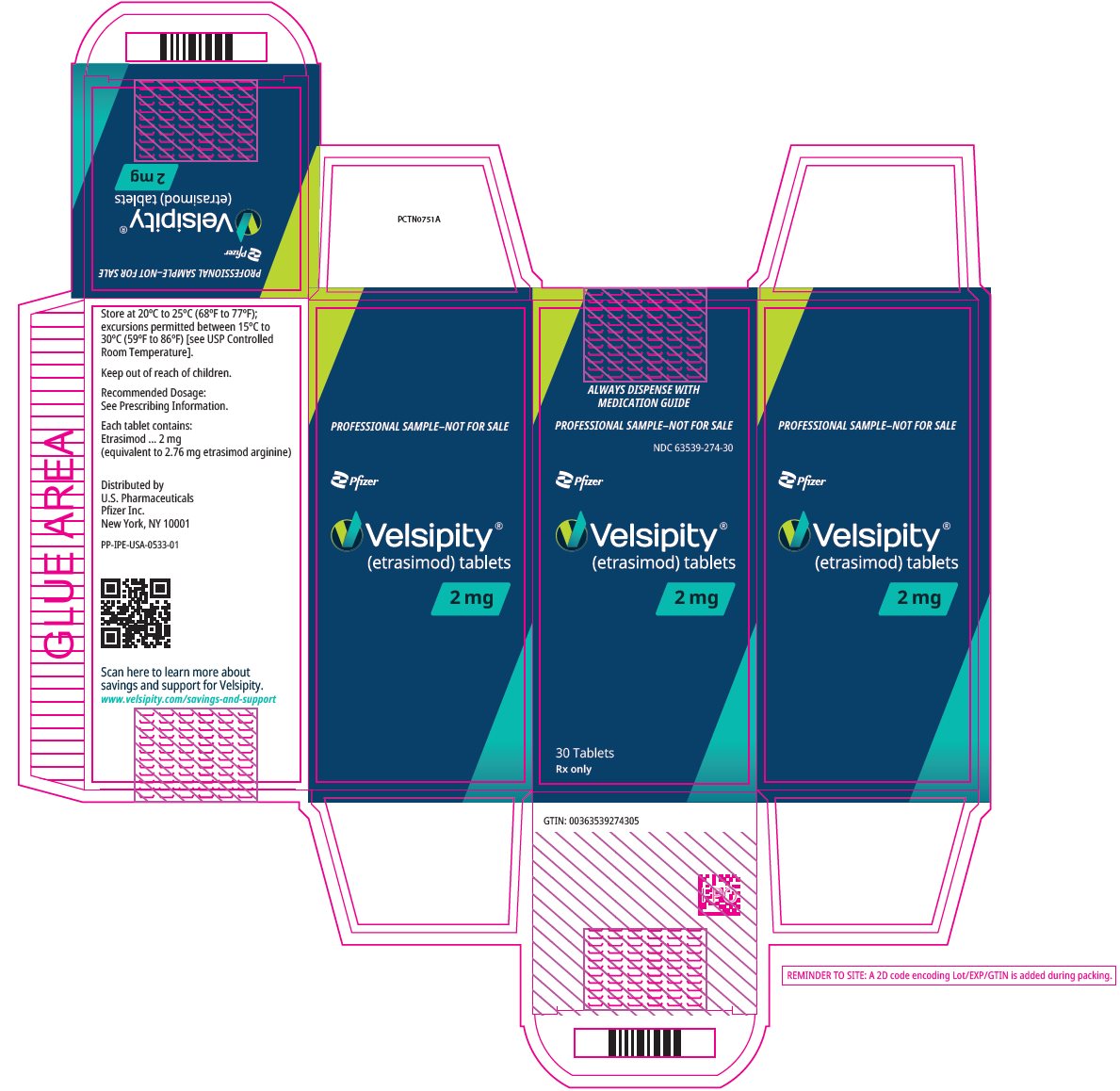 DRUG LABEL: Velsipity
NDC: 63539-274 | Form: TABLET, FILM COATED
Manufacturer: U.S. Pharmaceuticals
Category: prescription | Type: HUMAN PRESCRIPTION DRUG LABEL
Date: 20260203

ACTIVE INGREDIENTS: ETRASIMOD ARGININE 2 mg/1 1
INACTIVE INGREDIENTS: MAGNESIUM STEARATE; MANNITOL; MICROCRYSTALLINE CELLULOSE; SODIUM STARCH GLYCOLATE TYPE A; FD&C BLUE NO. 1 ALUMINUM LAKE; FD&C BLUE NO. 2 ALUMINUM LAKE; FD&C YELLOW NO. 5 ALUMINUM LAKE; POLYETHYLENE GLYCOL 3350; POLYVINYL ALCOHOL, UNSPECIFIED; TALC; TITANIUM DIOXIDE

HIGHLIGHTS OF PRESCRIBING INFORMATION

These highlights do not include all the information needed to use VELSIPITY safely and effectively. See full prescribing information for VELSIPITY.
VELSIPITY™ (etrasimod) tablets, for oral use
Initial U.S. Approval: 2023

1 INDICATIONS AND USAGE

VELSIPITY is a sphingosine 1-phosphate receptor modulator indicated for the treatment of moderately to severely active ulcerative colitis in adults. (1)

2 DOSAGE AND ADMINISTRATION

- Assessments are required prior to initiating VELSIPITY. (2.1)
- The recommended dosage is 2 mg orally once daily. (2.2)

3 DOSAGE FORMS AND STRENGTHS

Tablets: 2 mg of etrasimod (3)

4 CONTRAINDICATIONS

- In the last 6 months, experienced myocardial infarction, unstable angina pectoris, stroke, transient ischemic attack, decompensated heart failure requiring hospitalization, or Class III or IV heart failure. (4, 5.2)
- History or presence of Mobitz type II second-degree or third-degree atrioventricular (AV) block, sick sinus syndrome, or sino-atrial block, unless the patient has a functioning pacemaker. (4, 5.2)

5 WARNINGS AND PRECAUTIONS

- Infections: May increase the risk of infections. Obtain a complete blood count (CBC) before initiation of treatment. Monitor for infection during treatment and for 5 weeks after discontinuation. Consider interruption of treatment if a serious infection develops. Avoid use of live attenuated vaccines during and for up to 5 weeks after treatment. (5.1)
- Bradyarrhythmia and Atrioventricular Conduction Delays: May result in a transient decrease in heart rate and AV conduction delays. Obtain an electrocardiogram (ECG) to assess for preexisting cardiac conduction abnormalities before starting treatment. Consider cardiology consultation for conduction abnormalities or concomitant use with other drugs that decrease heart rate. (2.1, 5.2, 7)
- Liver Injury: Elevations of aminotransferases may occur. Obtain transaminase and bilirubin levels before initiating VELSIPITY. Discontinue if significant liver injury is confirmed. (2.1, 5.3)
- Macular Edema: May increase the risk of macular edema. Obtain a baseline evaluation of the fundus, including the macula, near the start of treatment with VELSIPITY. Periodically conduct an evaluation of the fundus, including the macula, while on therapy and any time there is a change in vision. Consider discontinuing VELSIPITY if macular edema develops. (2.1, 5.4)
- Increased Blood Pressure: Monitor blood pressure during treatment. (5.5)
- Fetal Risk: May cause fetal harm. Advise females of reproductive potential of the potential risk to a fetus and to use effective contraception during treatment and for one week after stopping VELSIPITY. (5.6, 8.3)
- Cutaneous Malignancies: Obtain a skin examination prior to or shortly after the start of treatment and periodically during treatment, especially if risk factors. Promptly evaluate suspicious skin lesions. (2.1, 5.7)
- Posterior Reversible Encephalopathy Syndrome (PRES): If symptoms develop, obtain a physical and neurological exam, and consider MRI. (5.8)
- Respiratory Effects: May cause a decline in pulmonary function. Assess pulmonary function (e.g., spirometry) if clinically indicated. (5.9)
- Unintended Additive Immune System Effects from Prior Treatment with Immunosuppressive or Immune-Modulating Drugs: Consider the half-life and mode of action of prior therapies. (5.10)
- Immune System Effects After Stopping VELSIPITY: If using concomitant immunosuppressants, monitor patients for infectious complications for up to 5 weeks after the last dose of VELSIPITY. (5.11)

6 ADVERSE REACTIONS

Most common adverse reactions (incidence ≥5%) are: headache, elevated liver tests, and dizziness. (6.1)

To report SUSPECTED ADVERSE REACTIONS, contact Pfizer Inc. at 1-800-438-1985 or FDA at 1-800-FDA-1088 or www.fda.gov/medwatch.

7 DRUG INTERACTIONS

See full prescribing information for a list of clinically important drug interactions. (7)

8 USE IN SPECIFIC POPULATIONS

Severe Hepatic Impairment: Use is not recommended. (8.6)

FULL PRESCRIBING INFORMATION

1 INDICATIONS AND USAGE

VELSIPITY is indicated for the treatment of moderately to severely active ulcerative colitis (UC) in adults.

2 DOSAGE AND ADMINISTRATION

2.1 Assessments, Medications, and Vaccinations Prior to First Dose of VELSIPITY

Before initiation of treatment with VELSIPITY, assess the following:

Complete Blood Count

Obtain a recent (i.e., within the last 6 months or after discontinuation of prior UC therapy) complete blood count (CBC), including lymphocyte count [see Warnings and Precautions (5.1)].

Cardiac Evaluation

Obtain an electrocardiogram (ECG) to determine whether preexisting conduction abnormalities are present. In patients with certain preexisting conditions, advice from a cardiologist should be sought [see Warnings and Precautions (5.2)].

Liver Function Tests

Obtain recent (i.e., within the last 6 months) transaminase and bilirubin levels [see Warnings and Precautions (5.3)].

Ophthalmic Assessment

Obtain a baseline evaluation of the fundus, including the macula, near the start of treatment with VELSIPITY [see Warnings and Precautions (5.4)].

Skin Examination

Obtain a skin examination prior to or shortly after initiation of VELSIPITY. If a suspicious skin lesion is observed, it should be promptly evaluated [see Warnings and Precautions (5.7)].

Current or Prior Medications

- Determine if patients are taking drugs that could slow heart rate or atrioventricular (AV) conduction [see Warnings and Precautions (5.2) and Drug Interactions (7)].
- If patients are taking anti-neoplastic, immune-modulating, or non-corticosteroid immunosuppressive therapies, or if there is a history of prior use of these drugs, consider possible unintended additive immunosuppressive effects before initiating treatment with VELSIPITY [see Warnings and Precautions (5.10) and Drug Interactions (7)].

Vaccinations

Patients without a healthcare professional-confirmed history of varicella (chickenpox) or without documentation of a full course of vaccination against varicella zoster virus (VZV) should be tested for antibodies to VZV before initiating VELSIPITY; VZV vaccination of antibody-negative patients is recommended prior to commencing treatment with VELSIPITY.

If live attenuated vaccine immunizations are required, administer at least 4 weeks prior to initiation of VELSIPITY.

Update immunizations in agreement with current immunization guidelines prior to initiating VELSIPITY therapy [see Warnings and Precautions (5.1)].

2.2 Recommended Dosage

- The recommended dosage of VELSIPITY is 2 mg orally once daily.
- Swallow the tablet whole, with or without food [see Clinical Pharmacology (12.3)].
- If a dose is missed, take the missed dose at the next scheduled time; do not double the next dose.

3 DOSAGE FORMS AND STRENGTHS

Tablets: 2 mg of etrasimod as a round, green, film-coated tablet, debossed with “ETR” on one side and “2” on the other side.

4 CONTRAINDICATIONS

VELSIPITY is contraindicated in patients who:

- In the last 6 months, have experienced a myocardial infarction, unstable angina pectoris, stroke, transient ischemic attack (TIA), decompensated heart failure requiring hospitalization, or Class III or IV heart failure [see Warnings and Precautions (5.2)].
- Have a history or presence of Mobitz type II second-degree or third-degree AV block, sick sinus syndrome, or sino-atrial block, unless the patient has a functioning pacemaker [see Warnings and Precautions (5.2)].

5 WARNINGS AND PRECAUTIONS

5.1 Infections

Risk of Infections

VELSIPITY causes a mean reduction in peripheral blood lymphocyte count to approximately 45% of baseline values at Week 52 because of reversible sequestration of lymphocytes in lymphoid tissues [see Clinical Pharmacology (12.2)]. VELSIPITY may, therefore, increase the susceptibility to infections. Life-threatening and rare fatal infections have been reported in association with other sphingosine 1-phosphate (S1P) receptor modulators.

Before initiating treatment, obtain a recent (i.e., within 6 months or after discontinuation of prior UC therapy) CBC, including lymphocyte count.

Delay initiation of VELSIPITY in patients with an active infection until the infection is resolved.

In UC-1, the overall rate of infections in subjects treated with VELSIPITY was 24.9% compared to 22.2% in subjects who received placebo. In pooled data from UC-2 and UC-3, the overall rate of infections in subjects treated with VELSIPITY was 14.0% compared to 11.8% in subjects who received placebo. The most common infections were urinary tract infections and herpes viral infections in UC-1, and urinary tract infections in UC-2 and UC-3 [see Adverse Reactions (6.1)].

The proportion of subjects treated with VELSIPITY who experienced lymphocyte counts less than 0.2 x 10^9/L was 5.5% in UC-1 and 0.6% in UC-2 and UC-3. These events did not lead to treatment discontinuation. Peripheral blood absolute lymphocyte counts returned to the normal range in 90% of subjects within 4 to 5 weeks of stopping therapy [see Clinical Pharmacology (12.2)].

Consider interruption of treatment with VELSIPITY if a patient develops a serious infection.

Because residual pharmacodynamic effects, such as lowering effects on peripheral lymphocyte count, may persist up to 5 weeks after discontinuation of VELSIPITY, vigilance for infection should be continued throughout this period.

Progressive Multifocal Leukoencephalopathy

Progressive multifocal leukoencephalopathy (PML) is an opportunistic viral infection of the brain caused by the JC virus (JCV) that typically occurs in patients who are immunocompromised, and that usually leads to death or severe disability. Typical symptoms associated with PML are diverse, progress over days to weeks, and include progressive weakness on one side of the body or clumsiness of limbs, disturbance of vision, and changes in thinking, memory, and orientation leading to confusion and personality changes.

PML has been reported in multiple sclerosis (MS) patients treated with S1P receptor modulators and has been associated with some risk factors (e.g., immunocompromised patients, polytherapy with immunosuppressants, and duration of use). Based on data from patients with MS, longer treatment duration increases the risk of PML in patients treated with S1P receptor modulators, and the majority of PML cases have occurred in patients treated with S1P receptor modulators for at least 18 months. VELSIPITY is not indicated for the treatment of MS. Physicians should be vigilant for clinical symptoms or unexplained neurologic findings that may be suggestive of PML. MRI findings may be apparent before clinical signs or symptoms. If PML is suspected, treatment with VELSIPITY should be suspended until PML has been excluded by an appropriate diagnostic evaluation.

If PML is confirmed, discontinue treatment with VELSIPITY.

Immune reconstitution inflammatory syndrome (IRIS) has been reported in MS patients treated with S1P receptor modulators who developed PML and subsequently discontinued treatment. IRIS presents as a clinical decline in the patient’s condition that may be rapid, can lead to serious neurological complications or death, and is often associated with characteristic changes on MRI. The time to onset of IRIS in patients with PML was generally within a few months after S1P receptor modulator discontinuation. Monitoring for development of IRIS and appropriate treatment of the associated inflammation should be undertaken.

Herpes Viral Infections

Herpes simplex encephalitis, varicella zoster meningitis, and localized herpes viral infections have been reported with S1P receptor modulators. In UC-1, herpes zoster was reported in 0.7% of subjects treated with VELSIPITY and in none of the subjects who received placebo. Patients without a healthcare professional-confirmed history of varicella (chickenpox), or without documentation of a full course of vaccination against varicella zoster virus (VZV), should be tested for antibodies to VZV before initiating VELSIPITY (see Vaccinations).

Cryptococcal Infection

Cases of fatal cryptococcal meningitis (CM) and disseminated cryptococcal infections have been reported with S1P receptor modulators. Physicians should be vigilant for clinical symptoms or signs of CM. Patients with symptoms or signs consistent with a cryptococcal infection should undergo prompt diagnostic evaluation and treatment. VELSIPITY treatment should be suspended until a cryptococcal infection has been excluded. If CM is diagnosed, appropriate treatment should be initiated.

Prior and Concomitant Treatment with Anti-neoplastic, Immune-modulating, or Non-corticosteroid Immunosuppressive Therapies

VELSIPITY has not been studied in combination with anti-neoplastic, immune-modulating, or non-corticosteroid immunosuppressive therapies. Avoid concomitant administration of these therapies with VELSIPITY and in the weeks following administration because of the risk of additive immunosuppressive effects [see Warnings and Precautions (5.10)].

Vaccinations

Patients without a healthcare professional-confirmed history of varicella (chickenpox) or without documentation of a full course of vaccination against varicella zoster virus (VZV) should be tested for antibodies to VZV before initiating VELSIPITY. A full course of VZV vaccination of antibody-negative patients is recommended prior to commencing treatment with VELSIPITY, following which initiation of treatment with VELSIPITY should be postponed for 4 weeks to allow the full effect of vaccination to occur.

No clinical data are available on the safety and efficacy of vaccinations in patients taking VELSIPITY. Vaccinations may be less effective if administered during VELSIPITY treatment.

If live attenuated vaccine immunizations are required, administer at least 4 weeks prior to initiation of VELSIPITY. Avoid the use of live attenuated vaccines during and for 5 weeks after treatment with VELSIPITY.

Update immunizations in agreement with current immunization guidelines prior to initiating VELSIPITY therapy.

5.2 Bradyarrhythmia and Atrioventricular Conduction Delays

Initiation of VELSIPITY may result in a transient decrease in heart rate and AV conduction delays [see Clinical Pharmacology (12.2)].

Reduction in Heart Rate

Initiation of VELSIPITY may result in a transient decrease in heart rate. After the first dose of VELSIPITY 2 mg, subjects with UC experienced the greatest mean decrease from baseline in heart rate of 7.2 bpm at Hour 3 in UC-1 and Hour 2 in UC-2.

In UC-1, bradycardia was reported on the day of treatment initiation in 1% of subjects treated with VELSIPITY compared to none in subjects who received placebo. On Day 2, bradycardia was reported in 1 subject (0.3%) treated with VELSIPITY compared to none in subjects who received placebo. In UC-2 and UC-3, bradycardia was reported on the day of treatment initiation in 2.9% of subjects treated with VELSIPITY compared to none in subjects who received placebo. On Day 2, bradycardia was reported in 1 subject (0.3%) treated with VELSIPITY compared to none in subjects who received placebo. Subjects who experienced bradycardia were generally asymptomatic. Few subjects experienced symptoms, such as dizziness, and these symptoms resolved without intervention.

Atrioventricular Conduction Delays

Initiation of VELSIPITY may result in transient AV conduction delays.

On the day of treatment initiation of VELSIPITY 2 mg, first- or second-degree Mobitz type I AV blocks were observed in 0.7% of VELSIPITY-treated subjects compared to none in placebo in UC-1, and in 0.8% of VELSIPITY-treated subjects compared to none in placebo in UC-2 and UC-3. In UC-1, UC-2, and UC-3, Mobitz type II second- or third-degree AV blocks were not reported in VELSIPITY-treated subjects.

If treatment with VELSIPITY is considered, advice from a cardiologist should be sought for those individuals:

- With significant QT prolongation (QTcF ≥450 msec in males, ≥470 msec in females)
- With arrhythmias requiring treatment with Class Ia or Class III anti-arrhythmic drugs or QT prolonging drugs [see Drug Interactions (7)]
- With unstable ischemic heart disease, Class I or II heart failure, history of cardiac arrest, cerebrovascular disease, or uncontrolled hypertension [see Contraindications (4)]
- With resting heart rate of less than 50 bpm
- With history of symptomatic bradycardia, recurrent cardiogenic syncope, or severe untreated sleep apnea
- With history of Mobitz type I second-degree AV block, unless the patient has a functioning pacemaker [see Contraindications (4)]

5.3 Liver Injury

Elevations of aminotransferases may occur in patients receiving VELSIPITY. In UC-1, elevations of alanine transaminase (ALT) greater than 3-fold the upper limit of normal (ULN) occurred in 4.5% of subjects who received VELSIPITY and 2.1% of subjects who received placebo. In UC-2 and UC-3, elevations of ALT greater than 3-fold the ULN occurred in 2.5% of subjects who received VELSIPITY and 0.5% of subjects who received placebo.

Obtain transaminase and bilirubin levels, if not recently available (i.e., within last 6 months), before initiation of VELSIPITY.

Obtain transaminases and bilirubin in patients who develop symptoms suggestive of hepatic dysfunction, such as unexplained nausea, vomiting, abdominal pain, fatigue, anorexia, or jaundice and/or dark urine. Discontinue VELSIPITY if significant liver injury is confirmed.

5.4 Macular Edema

S1P receptor modulators, including VELSIPITY, have been associated with an increased risk of macular edema. Obtain a baseline evaluation of the fundus, including the macula, near the start of treatment with VELSIPITY. Periodically conduct an evaluation of the fundus, including the macula, while on therapy and any time there is a change in vision.

Macular edema over an extended period of time (i.e., 6 months) can lead to permanent visual loss. Consider discontinuing VELSIPITY if macular edema develops.

5.5 Increased Blood Pressure

In UC-1 and UC-2 and UC-3, subjects treated with VELSIPITY had an average increase of approximately 1 to 4 mm Hg in systolic blood pressure and approximately 1 to 2 mm Hg in diastolic blood pressure compared to <1.5 mm Hg and <1 mm Hg in subjects receiving placebo, respectively. The increase was first detected after 2 weeks of treatment and remained within the specified average range of BP increases throughout treatment. Hypertension was reported as an adverse reaction in UC-1 [see Adverse Reactions (6.1)].

Monitor blood pressure during treatment with VELSIPITY and manage appropriately.

5.6 Fetal Risk

Based on animal studies, VELSIPITY may cause fetal harm when administered to a pregnant woman. In animal reproduction studies conducted in rats and rabbits, embryofetal toxicity was observed with administration of etrasimod at clinically relevant doses. Advise pregnant women and females of reproductive potential of the potential risk to a fetus. Advise females of reproductive potential to use effective contraception to avoid pregnancy during and for one week after stopping VELSIPITY [see Use in Specific Populations (8.1, 8.3)].

5.7 Cutaneous Malignancies

The risk of cutaneous malignancies (including basal cell carcinoma, squamous cell carcinoma, and melanoma) is increased in patients treated with S1P receptor modulators in controlled trials. Kaposi’s sarcoma and Merkel cell carcinoma have also been reported in patients treated with S1P receptor modulators in the postmarketing setting.

Skin examinations are recommended prior to or shortly after the start of treatment and periodically thereafter for all patients, particularly those with risk factors for skin cancer. Providers and patients are advised to monitor for suspicious skin lesions. If a suspicious skin lesion is observed, it should be promptly evaluated. As usual for patients with increased risk for skin cancer, exposure to sunlight and ultraviolet (UV) light should be limited by wearing protective clothing and using a sunscreen with a high protection factor. Concomitant phototherapy with UV-B radiation or PUVA-photochemotherapy is not recommended in patients taking VELSIPITY.

5.8 Posterior Reversible Encephalopathy Syndrome

Rare cases of posterior reversible encephalopathy syndrome (PRES) have been reported in patients receiving S1P receptor modulators. If a patient develops any neurological or psychiatric symptoms/signs (e.g., cognitive deficits, behavioral changes, cortical visual disturbances, or any other neurological cortical symptoms/signs), any symptom/sign suggestive of an increase of intracranial pressure, or accelerated neurological deterioration, the physician should promptly schedule a complete physical and neurological examination and should consider an MRI. Symptoms of PRES are usually reversible but may evolve into ischemic stroke or cerebral hemorrhage. Delay in diagnosis and treatment may lead to permanent neurological sequelae. If PRES is suspected, discontinue treatment with VELSIPITY.

5.9 Respiratory Effects

Reductions in absolute forced expiratory volume over 1 second (FEV1) were observed in subjects treated with VELSIPITY as early as 3 months after treatment initiation. In UC-1, the decline in absolute FEV1 from baseline in subjects treated with VELSIPITY compared to placebo was 79 mL (95% CI: -152, -5) at 3 months. In UC-2, reductions in absolute FEV1 were not observed. There is insufficient information to determine the reversibility of the decrease in FEV1 after drug discontinuation. In UC-1 and UC-2, subjects with UC and asthma and/or chronic obstructive pulmonary disease were treated with VELSIPITY; however, interpretation of changes in pulmonary function test measures in this population are limited due to small sample sizes. Spirometric evaluation of respiratory function should be performed during therapy with VELSIPITY if clinically indicated.

5.10 Unintended Additive Immune System Effects from Prior Treatment with Immunosuppressive or Immune-Modulating Drugs

When switching to VELSIPITY from drugs with prolonged immune effects, consider the half-life and mode of action of these drugs to avoid unintended additive immunosuppressive effects [see Drug Interactions (7)].

5.11 Immune System Effects After Stopping VELSIPITY

After stopping VELSIPITY, lymphocyte counts returned to the normal range in 90% of subjects within 4 to 5 weeks of stopping VELSIPITY [see Clinical Pharmacology (12.2)]. Use of immunosuppressants within this period may lead to an additive effect on the immune system, and therefore monitor patients receiving concomitant immunosuppressants for infectious complications up to 5 weeks after the last dose of VELSIPITY [see Drug Interactions (7)].

6 ADVERSE REACTIONS

The following serious adverse reactions are described elsewhere in the labeling:

- Infections [see Warnings and Precautions (5.1)]
- Bradyarrhythmia and Atrioventricular Conduction Delays [see Warnings and Precautions (5.2)]
- Liver Injury [see Warnings and Precautions (5.3)]
- Macular Edema [see Warnings and Precautions (5.4)]
- Increased Blood Pressure [see Warnings and Precautions (5.5)]
- Fetal Risk [see Warnings and Precautions (5.6)]
- Cutaneous Malignancies [see Warnings and Precautions (5.7)]
- Posterior Reversible Encephalopathy Syndrome [see Warnings and Precautions (5.8)]
- Respiratory Effects [see Warnings and Precautions (5.9)]
- Unintended Additive Immune System Effects from Prior Treatment with Immunosuppressive or Immune-Modulating Drugs [see Warnings and Precautions (5.10)]
- Immune System Effects After Stopping VELSIPITY [see Warnings and Precautions (5.11)]

6.1 Clinical Trials Experience

Because clinical trials are conducted under widely varying conditions, adverse reaction rates observed in the clinical trials of a drug cannot be directly compared to rates in the clinical trials of another drug and may not reflect the rates observed in clinical practice.

The safety of VELSIPITY 2 mg once daily in subjects with moderately to severely active ulcerative colitis was evaluated in two randomized, placebo-controlled studies of 52 weeks (UC-1) and 12 weeks (UC-2) duration [see Clinical Studies (14)]. Additional safety data were obtained from a randomized, double-blind, placebo-controlled dose-finding study of 12 weeks duration (UC-3).

In the 52-week study (UC-1), 433 subjects were enrolled of whom 289 received VELSIPITY 2 mg once daily. In the 12-week studies (UC-2 and UC-3), 458 subjects were enrolled of whom 288 received VELSIPITY 2 mg once daily.

Table 1 summarizes the adverse reactions reported in at least 2% of subjects and at a higher rate than placebo during UC-1.

Table 1: Adverse Reactions [Reported in at least 2% of subjects and at a higher rate than placebo.] in Subjects with Ulcerative Colitis in a Placebo-Controlled 52-Week Study (UC-1)
Adverse Reaction | VELSIPITY; 2 mg Once Daily; N = 289; % | Placebo; N = 144; %
Headache [Headache includes related terms headache, migraine, and tension headache.] | 9 | 5
Elevated liver tests [Elevated liver tests includes related terms ALT increased, AST increased, blood alkaline phosphatase increased, cholestasis, GGT increased, hepatic enzyme increased, hyperbilirubinemia, liver function test increased, and transaminases increased.] | 6 | 5
Dizziness [Dizziness includes related terms dizziness, dizziness exertional, and dizziness postural.] | 5 | 2
Arthralgia | 4 | 2
Hypertension [Hypertension includes related terms hypertension, and blood pressure increased.] | 3 | 1
Urinary tract infection [Urinary tract infection includes related terms urinary tract infection and cystitis.] | 3 | 2
Nausea | 3 | 1
Hypercholesterolemia [Hypercholesterolemia includes related terms hypercholesterolemia and blood cholesterol increased.] | 3 | 0
Herpes viral infection [Herpes viral infection includes related terms herpes zoster, oral herpes, and herpes simplex.] | 2 | 1

Table 2 summarizes the adverse reactions reported in at least 2% of subjects and at a higher rate than placebo during UC-2 and UC-3.

Table 2: Adverse Reactions [Reported in at least 2% of subjects and at a higher rate than placebo.] in Subjects with Ulcerative Colitis in Placebo-Controlled 12-Week Studies (UC-2 and UC-3)
Adverse Reaction | VELSIPITY; 2 mg Once Daily; N = 288; % [Study-size adjusted % for each group are based on the Mantel-Haenszel weights.] | Placebo; N = 170; %
Headache [Headache includes related terms headache, migraine, and sinus headache.] | 6 | 4
Elevated liver tests [Elevated liver tests includes related terms ALT increased, AST increased, blood alkaline phosphatase increased, blood bilirubin increased, cholestasis, GGT increased, hepatic enzyme increased, hepatic function abnormal, liver function test abnormal, and transaminases increased.] | 5 | <1
Nausea | 4 | 2
Bradycardia [Bradycardia includes related terms bradycardia, sinus bradycardia, and heart rate decreased.] | 3 | 0
Urinary tract infection [Urinary tract infection includes related terms urinary tract infection, cystitis, and genitourinary tract infection.] | 3 | 0

Ophthalmologic Findings

In UC-1, for subjects with a baseline and follow-up examination, a decrease in visual acuity was reported in 2.6% (4/156) of subjects who received VELSIPITY and no subjects who received placebo [see Warnings and Precautions (5.4)].

7 DRUG INTERACTIONS

Etrasimod is primarily metabolized by CYP2C8, CYP2C9, and CYP3A4. Table 3 includes drugs with clinically important drug interactions when administered concomitantly with VELSIPITY and instructions for preventing or managing them. Consult the labeling of concomitantly used drugs to obtain further information.

The effect of concomitant use of VELSIPITY with a combination of separate drugs that are moderate to strong inhibitors or inducers of either CYP2C8, CYP2C9, or CYP3A4 is unknown. However, based on the information below, a similar clinically significant change in exposure cannot be ruled out when two or more metabolic pathways are affected.

Table 3: Drugs That Affect VELSIPITY CYP-Mediated Metabolic Pathways
Anti-Arrhythmic Drugs and QT Prolonging Drugs
Clinical Impact | A transient decrease in heart rate and AV conduction delays may occur when initiating VELSIPITY [see Warnings and Precautions (5.2)].; Because of the potential additive effect on heart rate, VELSIPITY may increase the risk of QT prolongation and Torsades de Pointes with concomitant use of Class Ia and Class III anti-arrhythmic drugs and QT prolonging drugs.
Prevention or; Management | Seek the advice of a cardiologist before initiating VELSIPITY treatment with Class Ia (e.g., quinidine, procainamide), Class III anti-arrhythmic drugs (e.g., amiodarone, sotalol), or other drugs that prolong the QT interval.
Beta-Blockers or Calcium Channel Blockers
Clinical Impact | A transient decrease in heart rate and AV conduction delays may occur when initiating VELSIPITY [see Warnings and Precautions (5.2)].; Concomitant use of VELSIPITY in patients receiving stable beta blocker treatment did not result in additive effects on heart rate reduction [see Clinical Pharmacology (12.2)]. However, the risk of additive heart rate reduction following initiation of beta blocker therapy with stable VELSIPITY treatment or concomitant use with other drugs that may decrease heart rate is unknown.
Prevention or; Management | VELSIPITY can be initiated in patients receiving stable doses of beta blocker treatment.; Seek the advice of a cardiologist before initiating a beta blocker in a patient receiving stable VELSIPITY treatment or concomitant use with other drugs that may decrease heart rate (e.g., calcium channel blockers).
Anti-Neoplastic, Immune-Modulating, or Non-Corticosteroid Immunosuppressive Therapies
Clinical Impact | Risk of additive immune system effects with VELSIPITY; VELSIPITY has not been studied in combination with anti-neoplastic, immune-modulating, or non-corticosteroid immunosuppressive therapies.
Prevention or; Management | Avoid concomitant administration during and in the weeks following administration of VELSIPITY. When switching from drugs with prolonged immune effects, consider the half-life and mode of action of these drugs to avoid unintended additive immunosuppressive effects [see Warnings and Precautions (5.10)].
Moderate to Strong Inhibitors of CYP2C9 and CYP3A4
Clinical Impact | Increased exposure of etrasimod was observed with concomitant use with a drug that is a moderate inhibitor of CYP2C9 and a moderate inhibitor of CYP3A4 (i.e., fluconazole) [see Clinical Pharmacology (12.3)].
Prevention or; Management | Concomitant use with a drug that is a moderate to strong inhibitor of CYP2C9 and a moderate to strong inhibitor of CYP3A4 is not recommended.
CYP2C9 Poor Metabolizers Using Moderate to Strong Inhibitors of CYP2C8 or CYP3A4
Clinical Impact | Increased exposure of etrasimod in patients who are CYP2C9 poor metabolizers is expected with concomitant use of moderate to strong inhibitors of CYP2C8 or CYP3A4 [see Clinical Pharmacology (12.3, 12.5)].
Prevention or; Management | Concomitant use not recommended.
Rifampin
Clinical Impact | Concomitant use with a drug that is a combined CYP3A4 (strong), CYP2C8 (moderate) and CYP2C9 (moderate) inducer (i.e., rifampin) decreases exposure to etrasimod [see Clinical Pharmacology (12.3)].
Prevention or; Management | Concomitant use not recommended.

8 USE IN SPECIFIC POPULATIONS

8.1 Pregnancy

Pregnancy Exposure Registry

There is a pregnancy exposure registry that monitors pregnancy outcomes in females exposed to VELSIPITY during pregnancy. Pregnant females exposed to VELSIPITY and healthcare providers are encouraged to contact the pregnancy registry by calling 1-800-616-3791.

Risk Summary

Based on findings from animal studies, VELSIPITY may cause fetal harm when administered to a pregnant woman. Available data from reports of pregnancies from the clinical development program with VELSIPITY are insufficient to identify a drug-associated risk of major birth defects, miscarriage or other adverse maternal or fetal outcomes. There are risks to the mother and the fetus associated with increased disease activity in women with inflammatory bowel disease during pregnancy (see Clinical Considerations).

In animal reproduction studies, administration of etrasimod during organogenesis produced adverse effects on development, including embryolethality and fetal malformations, in both rats and rabbits at maternal exposures 5 and 6 times, respectively, the exposure at the maximum recommended human dose (MRHD). Administration of VELSIPITY to pregnant rats during organogenesis through lactation resulted in decreased pup growth and viability at maternal exposures 5 times the exposure at the MRHD, as well as impaired reproductive performance in first generation offspring, including decreased implantations and increased pre-implantation loss at maternal exposures 24 times the exposure at the MRHD (see Data).

The background risk of major birth defects and miscarriage for the indicated population is unknown. All pregnancies have a background risk of birth defect, loss, or other adverse outcomes. In the U.S. general population, the estimated background risk of major birth defects and miscarriage in clinically recognized pregnancies is 2% to 4% and 15% to 20%, respectively.

Clinical Considerations

Disease-Associated Maternal and/or Embryo/Fetal Risk

Published data suggest that the risk of adverse pregnancy outcomes in women with inflammatory bowel disease is associated with increased disease activity. Adverse pregnancy outcomes include preterm delivery (before 37 weeks of gestation), low birth weight (less than 2500 g) infants, and small for gestational age at birth.

Data

Animal Data

In an embryo-fetal development study in pregnant rats, etrasimod was orally administered at 1, 2, or 4 mg/kg/day (5, 11, and 21 times the exposure at the MRHD of 2 mg, based on AUC comparison) during the period of organogenesis, from gestation day 6 to 17. No maternal toxicity was observed up to 21 times the exposure at the MRHD. Increased post-implantation loss with a corresponding decrease in the number of viable fetuses was observed at 4 mg/kg/day (21 times the exposure at the MRHD). Etrasimod-related fetal external and/or visceral malformations were noted at all dose levels (≥5 times the exposure at the MRHD).

In an embryo-fetal development study in pregnant rabbits, etrasimod was orally administered at 2, 10, or 20 mg/kg/day (0.8, 6, and 11 times the exposure at the MRHD of 2 mg, based on AUC comparison) during the period of organogenesis, from gestation day 7 to 20. Increased post-implantation loss with a corresponding decrease in the number of viable fetuses was observed at 10 and 20 mg/kg/day (6 and 11 times the exposure at the MRHD). Etrasimod-related fetal malformations including aortic arch defects and fused sternebrae were noted at 10 and/or 20 mg/kg/day (6 and 11 times the exposure at the MRHD). There were no adverse effects on embryofetal development at 2 mg/kg/day (less than the exposure at the MRHD).

In a pre- and post-natal development study in rats, etrasimod was orally administered at 0.4, 2, or 4 mg/kg/day (2, 10, and 24 times the exposure at the MRHD of 2 mg, based on AUC comparison) throughout pregnancy and lactation, from gestation day 6 through lactation day 20. Mortality during delivery and impaired maternal performance including increased post-implantation loss, increased number of females with stillborn pups, increased number of stillborn pups per litter, decreased viability index, and/or decreased lactation index was observed at 2 and 4 mg/kg/day (10 and 24 times the exposure at the MRHD). Etrasimod was detected in the plasma of F1 offspring, indicating exposure from the milk of the lactating dam. Decreased pup body weights were observed during the preweaning period at all dose levels (maternal exposures ≥2 times the exposure at the MRHD), and decreased pup viability was observed at 2 and 4 mg/kg/day (maternal exposures 10 and 24 times the exposure at the MRHD). Reduced fertility and reproductive performance including reduction in implantations and increased preimplantation loss in F1 offspring occurred at the highest dose tested (maternal exposures 24 times the exposure at the MRHD).

8.2 Lactation

Risk Summary

There are no data on the presence of etrasimod in human milk, the effects on the breastfed infant, or the effects of the drug on milk production. When etrasimod was orally administered to female rats during pregnancy and lactation, etrasimod was detected in the plasma of the offspring, suggesting excretion of etrasimod in milk.

The developmental and health benefits of breastfeeding should be considered along with the mother's clinical need for VELSIPITY and any potential adverse effects on the breastfed infant from VELSIPITY or from the underlying maternal condition.

8.3 Females and Males of Reproductive Potential

Based on animal data, VELSIPITY may cause fetal harm when administered to pregnant women [see Use in Specific Populations (8.1)].

Contraception

Females

Before initiation of VELSIPITY treatment, females of reproductive potential should be counseled on the potential for a serious risk to the fetus and the need for effective contraception during treatment with VELSIPITY and for one week following the last dose [see Warnings and Precautions (5.6) and Use in Specific Populations (8.1)].

8.4 Pediatric Use

The safety and effectiveness of VELSIPITY in pediatric patients have not been established.

8.5 Geriatric Use

Of the 577 VELSIPITY-treated subjects in the three clinical trials (UC-1, UC-2, and UC-3), 30 subjects (5%) were 65 years of age and older, while 3 subjects (<1%) were 75 years of age and older. Clinical studies of VELSIPITY did not include sufficient numbers of subjects aged 65 and older to determine whether they respond differently from younger adult subjects. The pharmacokinetics of etrasimod are similar in subjects 65 years of age and older compared to younger adult subjects [see Clinical Pharmacology (12.3)].

8.6 Hepatic Impairment

Etrasimod undergoes extensive hepatic metabolism. Exposure to etrasimod was similar in subjects with mild and moderate hepatic impairment (Child-Pugh A and B) compared to subjects with normal hepatic function; however, etrasimod exposure was increased in subjects with severe hepatic impairment (Child‑Pugh C) compared to subjects with normal hepatic function [see Clinical Pharmacology (12.3)].

Use of VELSIPITY in patients with severe hepatic impairment is not recommended. No dosage adjustment is needed in patients with mild to moderate hepatic impairment.

8.7 CYP2C9 Poor Metabolizers

Increased exposure of etrasimod in patients who are CYP2C9 poor metabolizers is expected with concomitant use of moderate to strong inhibitors of CYP2C8 or CYP3A4. Concomitant use of VELSIPITY is not recommended in these patients [see Clinical Pharmacology (12.3, 12.5)].

11 DESCRIPTION

VELSIPITY contains etrasimod, a sphingosine 1-phosphate (S1P) receptor modulator, supplied as etrasimod arginine.

Etrasimod arginine is a white, off-white to light brown solid that is slightly soluble in water. The chemical name of etrasimod arginine is L-Arginine, (3R)-7-[[4-cyclopentyl-3-(trifluoromethyl)phenyl]methoxy]-1,2,3,4-tetrahydrocyclopent[b]indole-3-acetate (1:1) having a molecular formula of C32H40F3N5O5 and a molecular weight of 631.69 g/mol.

The chemical structure of etrasimod arginine is:

VELSIPITY is supplied for oral administration as 2 mg tablets. Each tablet contains 2 mg etrasimod (equivalent to 2.76 mg etrasimod arginine) and the following inactive ingredients: magnesium stearate, mannitol, microcrystalline cellulose, and sodium starch glycolate, with a film coating containing FD&C blue #1/brilliant blue FCF aluminum lake, FD&C blue #2/indigo carmine aluminum lake, FD&C yellow #5/tartrazine aluminum lake, macrogol 4000 JP/PEG 3350, polyvinyl alcohol (partially hydrolyzed), talc, and titanium dioxide.

12 CLINICAL PHARMACOLOGY

12.1 Mechanism of Action

Etrasimod is a sphingosine 1-phosphate (S1P) receptor modulator that binds with high affinity to S1P receptors 1, 4, and 5 (S1P1,4,5). Etrasimod has minimal activity on S1P3 (25-fold lower than Cmax at the recommended dose) and no activity on S1P2. Etrasimod partially and reversibly blocks the capacity of lymphocytes to egress from lymphoid organs, reducing the number of lymphocytes in peripheral blood. The mechanism by which etrasimod exerts therapeutic effects in UC is unknown but may involve the reduction of lymphocyte migration into the intestines.

12.2 Pharmacodynamics

Reduction in Blood Lymphocyte Counts

VELSIPITY causes a reduction in peripheral blood lymphocyte count [see Warnings and Precautions (5.1)]. In UC-1 and UC-2, mean lymphocyte counts decreased to approximately 50% of baseline at 2 weeks (approximate mean blood lymphocyte counts 0.9 x 10^9/L) and the lower lymphocyte counts were maintained during treatment with VELSIPITY.

Dose-response relationship analysis indicates there is a dose-dependent reduction in blood lymphocyte counts. After discontinuing VELSIPITY 2 mg once daily, the median time for peripheral blood lymphocytes to return to the normal range was 2.6 weeks, with approximately 90% of subjects in the normal range within 4.7 weeks.

Reduction in Heart Rate and AV Conduction Delays

VELSIPITY may result in a transient decrease in heart rate and AV conduction upon treatment initiation [see Warnings and Precautions (5.2)]. In UC-1 and UC-2, the mean (SD) decrease in heart rate was 7.2 (8.98) bpm at 2 to 3 hours after the first dose of VELSIPITY on Day 1.

Cardiac Electrophysiology

At 2 times the maximum recommended dose, etrasimod does not cause clinically significant QTc interval prolongation.

Pulmonary Function

Reductions in absolute FEV1 were observed in subjects treated with VELSIPITY [see Warnings and Precautions (5.9)].

Drug Interaction Studies

No clinically significant differences in heart rate reduction were observed when etrasimod was used concomitantly with stable beta blocker treatment. The effect of concomitant use of etrasimod with a calcium channel blocker on heart rate reduction is unknown [see Drug Interactions (7)].

12.3 Pharmacokinetics

Etrasimod mean (SD) steady-state maximum plasma concentration (Cmax) was 113 (27.5) ng/mL and area under the time concentration curve at the dosing interval (AUCtau) was 2162 (488) ng*h/mL at the recommended dosage. Etrasimod Cmax and AUC are approximately dose proportional from 0.7 mg to 2 mg (0.35 times up to the recommended dosage). Etrasimod steady state is reached within 7 days with an accumulation of approximately 2- to 3-fold compared to the first dose.

Absorption

The median (range) time to reach etrasimod Cmax (Tmax) is approximately 4 hours (range 2 to 8 hours) after oral administration.

Effect of Food

No clinically significant differences in the pharmacokinetics of etrasimod were observed following administration of VELSIPITY with a high-fat meal (800 to 1000 calories) [see Dosage and Administration (2.2)].

Distribution

The mean apparent volume of distribution of etrasimod is 66 (24) L. Etrasimod plasma protein binding is 97.9%.

Elimination

The mean plasma elimination half-life (t1/2) of etrasimod is approximately 30 hours with an apparent steady-state oral clearance of approximately 1 L/h after oral administration.

Metabolism

Etrasimod is metabolized by oxidation and dehydrogenation mediated primarily by CYP2C8, CYP2C9, and CYP3A4, with a minor contribution by CYP2C19 and CYP2J2. Etrasimod also undergoes conjugation primarily mediated by UGTs, with a minor contribution by sulfotransferases. Unchanged etrasimod is the main circulating component in plasma.

Excretion

Approximately 82% of total radioactive etrasimod dose was recovered in the feces and 5% in the urine within 336 hours. Approximately 11% of administered radioactive dose was excreted as unchanged etrasimod in feces and none was excreted unchanged in urine.

Specific Populations

No clinically significant differences in the pharmacokinetics of etrasimod were observed based on age (>65 years), sex, body weight, race, ethnicity, disease (healthy subjects vs. subjects with ulcerative colitis), and severe renal impairment (eGFR ≤29 mL/min).

Patients with Hepatic Impairment

Etrasimod AUC increased by 13% in subjects with mild (Child-Pugh A), 29% in moderate (Child-Pugh B), and 57% in severe (Child-Pugh C) hepatic impairment, respectively, compared with subjects with normal liver function. No clinically significant difference in the unbound etrasimod AUC was observed [see Use in Specific Populations (8.6)].

Drug Interaction Studies

Clinical Studies

Combined moderate CYP2C9 and CYP3A4 inhibitors: Concomitant use of etrasimod with steady-state fluconazole (moderate CYP2C9 and CYP3A4 inhibitor) increased etrasimod AUC by 84% [see Drug Interactions (7)].

Combined CYP3A4 (strong), CYP2C8 (moderate) and CYP2C9 (moderate) inducers: Concomitant use of etrasimod with rifampin (strong CYP3A4, moderate CYP2C8, and CYP2C9 inducer) decreased etrasimod AUC by 49% [see Drug Interactions (7)].

Oral Contraceptives: No clinically significant differences in the pharmacokinetics and pharmacodynamics of oral contraceptive containing 30 mcg ethinyl estradiol and 150 mcg levonorgestrel were observed when used concomitantly with etrasimod.

Other Drugs: Itraconazole (a P-gp and strong CYP3A inhibitor) increased etrasimod AUC by 32%. Gemfibrozil (an inhibitor of OATP1B1 and OAT3 and a strong inhibitor of CYP2C8) increased etrasimod AUC by 36%. These effects are unlikely to be clinically significant.

In Vitro Studies

Based on in vitro studies, etrasimod is not an inhibitor of CYP1A2, CYP2B6, CYP2C8, CYP2C9, CYP2C19, CYP2D6, and CYP3A4, nor an inducer of CYP1A2, CYP2B6, and CYP3A4 at clinically relevant concentrations.

Etrasimod is not an inhibitor of UGT1A3, UGT1A4, UGT1A9, UGT2B7, or UGT2B17 in vitro.

Etrasimod is not a substrate or an inhibitor of P-gp, BCRP, BSEP, OATP1B1, OATP1B3, OAT1, OAT3, OCT1, OCT2, MATE1, and MATE2-K transporters.

12.5 Pharmacogenomics

CYP2C9 activity is decreased in individuals with genetic variants such as CYP2C9*2 and CYP2C9*3 alleles. The impact of CYP2C9 genetic variants on the pharmacokinetics of etrasimod has not been directly evaluated. CYP2C9 poor metabolizers (e.g., *2/*3, *3/*3) may have decreased clearance of etrasimod when VELSIPITY is used concomitantly with moderate to strong inhibitors of CYP2C8 or CYP3A4 [see Drug Interactions (7) and Use in Specific Populations (8.7)].

CYP2C9 intermediate metabolizers (e.g., *1/*2, *1/*3, *2/*2) may have decreased clearance of etrasimod when VELSIPITY is used concomitantly with moderate to strong inhibitors of CYP2C8 or CYP3A4; however, the effect on VELSIPITY exposure in CYP2C9 intermediate metabolizers with concomitant CYP2C8 or CYP3A4 inhibitors is not known.

The prevalence of the CYP2C9 poor metabolizer phenotype is approximately 2 to 3% in White populations, 0.5 to 4% in Asian populations, and <1% in African-American populations. Other decreased or nonfunctional CYP2C9 alleles (e.g., *5, *6, *8, *11) are more prevalent in African-American populations.

13 NONCLINICAL TOXICOLOGY

13.1 Carcinogenesis, Mutagenesis, Impairment of Fertility

Carcinogenesis

Oral carcinogenicity studies with etrasimod were conducted in mice and rats. In mice administered etrasimod (2, 6, or 20 mg/kg/day) for up to 104 weeks, there was an increase in hemangiosarcoma and hemangioma in males and females at 6 and 20 mg/kg/day. No increase in tumors was observed at the lowest tested dose of 2 mg/kg/day (approximately 19 times the exposure at the MRHD of 2 mg, based on AUC comparison). In rats, oral administration of etrasimod (2, 6, or 20 mg/kg/day) for up to 91 weeks did not result in an increase in tumors (male and female exposures 80 and 179 times, respectively, the exposure at the MRHD).

Mutagenesis

Etrasimod was negative in a battery of in vitro (Ames, chromosomal aberration in human peripheral blood lymphocytes) and in vivo (rat micronucleus) assays.

Impairment of Fertility

Etrasimod administered orally to male rats at 25, 100, or 200 mg/kg/day from pre-mating through mating had no adverse effects on male fertility at exposures up to 467 times the exposure at the MRHD of 2 mg, based on AUC comparison. Etrasimod administered orally to female rats at 1, 2, or 4 mg/kg/day from pre-mating to implantation had no adverse effects on female fertility at exposures up to 21 times the exposure at the MRHD.

14 CLINICAL STUDIES

The efficacy of VELSIPITY was evaluated in 2 randomized, double-blind, placebo-controlled clinical studies [UC-1 (NCT03945188) and UC-2 (NCT03996369)] in adult subjects with moderately to severely active ulcerative colitis who had an inadequate response, loss of response, or intolerance to one or more of the following treatment options: oral aminosalicylates, corticosteroids, thiopurines, Janus kinase (JAK) inhibitors, or biologic therapies (e.g., TNF blocker, anti-integrin, anti-IL12/23). UC-1 was a 52-week study and UC-2 was a 12-week study. In both studies, subjects were randomized to VELSIPITY or placebo and continued on treatment for the entire duration of the study.

Disease severity was assessed based on the modified Mayo score (mMS), a 3-component Mayo score (0 to 9) which consists of the following subscores (0 to 3 for each subscore): stool frequency (SF), rectal bleeding (RB), and findings on centrally read endoscopy score (ES). An ES of 2 was defined by marked erythema, lack of vascular pattern, any friability, and/or erosions, and a score of 3 was defined by spontaneous bleeding and ulceration.

Subjects in these studies may have received other concomitant UC therapies including stable daily doses of oral aminosalicylates and/or oral corticosteroids (≤20 mg/day prednisone, ≤9 mg/day budesonide, or equivalent steroid). Concomitant treatment with immunomodulators (e.g., thiopurines, methotrexate), biologic therapies, JAK inhibitors, rectal 5-ASA, or rectal corticosteroids was not permitted.

Endpoints and Results Study UC-1

In UC-1, efficacy was evaluated in 408 adult subjects with a baseline mMS of 5 to 9 (median of 7), including a centrally read endoscopy subscore of 2 or 3. Subjects were randomized 2:1 to receive VELSIPITY 2 mg or placebo administered orally once daily. Subjects had a mean age of 41 years (range 18 to 78 years); 45% were female; and 89% identified as White, 7% as Asian, 2% as Black or African American, 1% as American Indian or Alaska Native, and 1% did not report their racial group. A total of 30% of subjects had prior exposure to biologic/JAK inhibitors and a total of 14% of subjects had exposure to >1 biologic/JAK inhibitor. At baseline, 68% of subjects were receiving oral aminosalicylates and 31% of subjects were receiving oral corticosteroids.

The coprimary endpoints were the proportion of subjects achieving clinical remission at Week 12 and at Week 52. The secondary endpoints included the proportion of subjects achieving endoscopic improvement, histologic-endoscopic mucosal improvement, corticosteroid-free clinical remission, and maintenance of clinical remission (see Table 4).

Table 4: Proportion of Subjects with Ulcerative Colitis Meeting Efficacy Endpoints in UC-1 at Week 12 and at Week 52
Endpoints | Placebo | VELSIPITY | Treatment; Difference [Treatment difference (adjusted for stratification factors of prior biologic/JAK inhibitor exposure, corticosteroid use at baseline, and baseline mMS group).]; (95% CI)
Coprimary Endpoints
Clinical Remission [Clinical remission is defined as SF subscore of 0 or 1, RB subscore of 0, and ES ≤1 (excluding friability).] at Week 12
Total population | N = 134; 7% | N = 274; 27% | 20% [p <0.001.]; (13%, 27%)
No prior biologic/; JAK inhibitor exposure | N = 93; 10% | N = 194; 31%
Prior biologic/; JAK inhibitor exposure | N = 41; 2% | N = 80; 18%
Clinical Remission at Week 52
Total population | N = 134; 7% | N = 274; 32% | 26%; (19%, 33%)
No prior biologic/; JAK inhibitor exposure | N = 93; 8% | N = 194; 37%
Prior biologic/; JAK inhibitor exposure | N = 41; 5% | N = 80; 21%
Week 12 Endpoints
Endoscopic Improvement [Endoscopic improvement is defined as ES ≤1 (excluding friability).]
Total population | N = 134; 14% | N = 274; 35% | 21%; (13%, 29%)
No prior biologic/; JAK inhibitor exposure | N = 93; 18% | N = 194; 39%
Prior biologic/; JAK inhibitor exposure | N = 41; 5% | N = 80; 25%
Histologic-Endoscopic Mucosal Improvement [Histologic-endoscopic mucosal improvement is defined as ES ≤1 (excluding friability) with Geboes Index score <2.0, indicating no neutrophils in the epithelial crypts or lamina propria, no increase in eosinophils, and no crypt destruction, erosions, ulcerations, or granulation tissue.]
Total population | N = 134; 4% | N = 274; 21% | 17%; (11%, 23%)
No prior biologic/; JAK inhibitor exposure | N = 93; 6% | N = 194; 24%
Prior biologic/; JAK inhibitor exposure | N = 41; 0% | N = 80; 14%
Week 52 Endpoints
Endoscopic Improvement
Total population | N = 134; 10% | N = 274; 37% | 27%; (19%, 34%)
No prior biologic/; JAK inhibitor exposure | N = 93; 13% | N = 194; 40%
Prior biologic/; JAK inhibitor exposure | N = 41; 5% | N = 80; 30%
Histologic-Endoscopic Mucosal Improvement
Total population | N = 134; 8% | N = 274; 27% | 18%; (11%, 25%)
No prior biologic/; JAK inhibitor exposure | N = 93; 11% | N = 194; 28%
Prior biologic/; JAK inhibitor exposure | N = 41; 2% | N = 80; 23%
Corticosteroid-free Clinical Remission [Corticosteroid-free clinical remission is defined as clinical remission at Week 52 without receiving corticosteroids for at least 12 weeks prior to Week 52.]
Total population | N = 134; 7% | N = 274; 32% | 26%; (19%, 33%)
No prior biologic/; JAK inhibitor exposure | N = 93; 8% | N = 194; 37%
Prior biologic/; JAK inhibitor exposure | N = 41; 5% | N = 80; 21%
Maintenance of Clinical Remission [Maintenance of clinical remission is defined as achievement of clinical remission at both Week 12 and Week 52.]
Total population | N = 134; 2% | N = 274; 18% | 16%; (11%, 21%)
No prior biologic/; JAK inhibitor exposure | N = 93; 2% | N = 194; 22%
Prior biologic/; JAK inhibitor exposure | N = 41; 2% | N = 80; 10%
CI = confidence interval

The relationship of histologic-endoscopic mucosal improvement at Week 12 or Week 52 to disease progression and longer-term outcomes after Week 52 was not evaluated in Study UC-1.

Clinical Response

A greater proportion of subjects treated with VELSIPITY compared to placebo achieved clinical response, defined as a ≥2 point and ≥30% decrease from baseline in mMS, and a ≥1 point decrease from baseline in RB subscore or an absolute RB subscore ≤1 at Week 12 (62% vs 34%).

Stool Frequency and Rectal Bleeding Subscores

Decreases in SF subscores were observed as early as Week 2 and decreases in RB subscores were observed as early as Week 4 in subjects treated with VELSIPITY compared to placebo.

Endoscopic Assessment

Normalization of the endoscopic appearance of the mucosa (endoscopic remission) was defined as ES of 0. A greater proportion of subjects treated with VELSIPITY compared to placebo achieved endoscopic remission by Week 12 (15% vs 4%), Week 52 (26% vs 6%), and both Week 12 and Week 52 (11% vs 1%).

Endpoints and Results Study UC-2

In UC-2, efficacy was evaluated in 333 adult subjects with a baseline mMS of 5 to 9 (median of 7), including a centrally read endoscopy subscore of 2 or 3. Subjects were randomized 2:1 to receive VELSIPITY 2 mg or placebo administered orally once daily. Subjects had a mean age of 41 years (range 18 to 73 years); 41% were female; and 76% identified as White, 19% as Asian, 2% as American Indian or Alaska Native, 1% as Black or African American, and 2% as multiple racial groups or did not report their racial group. A total of 34% of subjects had prior exposure to biologic/JAK inhibitors and a total of 17% of subjects had exposure to >1 biologic/JAK inhibitor. At baseline, 66% of subjects were receiving oral aminosalicylates and 28% of subjects were receiving oral corticosteroids.

The primary endpoint was the proportion of subjects achieving clinical remission at Week 12. The secondary endpoints included the proportion of subjects achieving endoscopic improvement and histologic-endoscopic mucosal improvement at Week 12 (see Table 5).

Table 5: Proportion of Subjects with Ulcerative Colitis Meeting Efficacy Endpoints in UC-2 at Week 12
Endpoints | Placebo | VELSIPITY | Treatment; Difference [Treatment difference (adjusted for stratification factors of prior biologic/JAK inhibitor exposure, corticosteroid use at baseline, and baseline mMS group).]; (95% CI)
Clinical Remission [Clinical remission is defined as SF subscore of 0 or 1, RB subscore of 0, and ES ≤1 (excluding friability).]
Total population | N = 112; 15% | N = 221; 26% | 11% [p <0.05.]; (3%, 20%)
No prior biologic/; JAK inhibitor exposure | N = 74; 16% | N = 147; 30%
Prior biologic/; JAK inhibitor exposure | N = 38; 13% | N = 74; 19%
Endoscopic Improvement [Endoscopic improvement is defined as ES ≤1 (excluding friability).]
Total population | N = 112; 19% | N = 221; 30% | 12%; (3%, 21%)
No prior biologic/; JAK inhibitor exposure | N = 74; 19% | N = 147; 34%
Prior biologic/; JAK inhibitor exposure | N = 38; 18% | N = 74; 23%
Histologic-Endoscopic Mucosal Improvement [Endoscopic-histologic mucosal improvement is defined as ES ≤1 (excluding friability) with Geboes Index score <2.0, indicating no neutrophils in the epithelial crypts or lamina propria, no increase in eosinophils, and no crypt destruction, erosions, ulcerations, or granulation tissue.]
Total population | N = 112; 9% | N = 221; 16% | 8%; (1%, 15%)
No prior biologic/; JAK inhibitor exposure | N = 74; 11% | N = 147; 19%
Prior biologic/; JAK inhibitor exposure | N = 38; 5% | N = 74; 11%
CI = confidence interval

The relationship of histologic-endoscopic mucosal improvement at Week 12 to disease progression and longer-term outcomes after Week 12 was not evaluated in Study UC-2.

Clinical Response

A greater proportion of subjects treated with VELSIPITY compared to placebo achieved clinical response, defined as a ≥2 point and ≥30% decrease from baseline in mMS, and a ≥1 point decrease from baseline in RB subscore or an absolute RB subscore ≤1 at Week 12 (62% vs 41%).

Stool Frequency and Rectal Bleeding Subscores

Decreases in SF subscores were observed as early as Week 2 and decreases in RB subscores were observed as early as Week 4 in subjects treated with VELSIPITY compared to placebo.

Endoscopic Assessment

Normalization of the endoscopic appearance of the mucosa (endoscopic remission) was defined as ES of 0. A greater proportion of subjects treated with VELSIPITY compared to placebo achieved endoscopic remission by Week 12 (17% vs 8%).

16 HOW SUPPLIED/STORAGE AND HANDLING

How Supplied

VELSIPITY tablet is available as a round, green film-coated 2 mg etrasimod tablet, debossed with “ETR” on one side and “2” on the other side.

VELSIPITY tablets are packed in a child-resistant 100 mL white, round, high-density polyethylene (HDPE) bottle containing 4 g of silica gel desiccant integrated directly into the 45 mm polypropylene (PP) cap.

Dosage Form | Strength | Description | NDC Number
Tablets | 2 mg of etrasimod | 30 count bottle | 0069-0274-30

Storage and Handling

Store at 20°C to 25°C (68°F to 77°F); excursions permitted between 15°C to 30°C (59°F to 86°F) [see USP Controlled Room Temperature].

17 PATIENT COUNSELING INFORMATION

Advise the patient to read the FDA-approved patient labeling (Medication Guide).

Risk of Infections

Inform patients that they may be more likely to get infections, some of which could be life-threatening, when taking VELSIPITY and for 5 weeks after stopping it, and that they should contact their healthcare provider if they develop symptoms of infection [see Warnings and Precautions (5.1)]. Inform patients that prior or concomitant use of drugs that suppress the immune system may increase the risk of infection.

Advise patients that some vaccines containing live virus (live attenuated vaccines) should be avoided during treatment with VELSIPITY. Advise patients that if immunizations are planned, they should be administered at least 4 weeks prior to initiation of VELSIPITY. Inform patients that the use of live attenuated vaccines should be avoided during and for 5 weeks after treatment with VELSIPITY.

Cardiac Effects

Advise patients that initiation of VELSIPITY treatment may result in transient decrease in heart rate [see Warnings and Precautions (5.2)].

Liver Injury

Inform patients that VELSIPITY may increase liver enzymes. Advise patients that they should contact their healthcare provider if they have any unexplained nausea, vomiting, abdominal pain, fatigue, anorexia, or jaundice and/or dark urine [see Warnings and Precautions (5.3)].

Macular Edema

Advise patients that VELSIPITY may cause macular edema, and that they should obtain an eye exam near the start of treatment with VELSIPITY, have their eyes monitored periodically by an eye care professional while receiving therapy, and contact their healthcare provider if they experience any changes in their vision while taking VELSIPITY [see Warnings and Precautions (5.4)].

Fetal Risk

VELSIPITY may cause fetal harm. Advise females to immediately inform their healthcare provider of a known or suspected pregnancy [see Warnings and Precautions (5.6) and Use in Specific Populations (8.1)].

Advise females of reproductive potential to use effective contraception during treatment with VELSIPITY and for one week after stopping VELSIPITY [see Use in Specific Populations (8.3)].

Pregnancy and Pregnancy Registry

Advise patients that there is a pregnancy registry that monitors pregnancy outcomes in women exposed to VELSIPITY during pregnancy [see Use in Specific Populations (8.1)].

Cutaneous Malignancies

Advise patients to limit exposure to sunlight and ultraviolet (UV) light, wear protective clothing, and use a sunscreen with a high protection factor. Concomitant phototherapy with UV-B radiation or PUVA‑photochemotherapy is not recommended in patients taking VELSIPITY. If a suspicious skin lesion is observed, patients should immediately report it to their healthcare provider [see Warnings and Precautions (5.7)].

Posterior Reversible Encephalopathy Syndrome

Advise patients to immediately report to their healthcare provider any symptoms involving sudden onset of severe headache, altered mental status, visual disturbances, or seizure. Inform patients that delayed treatment could lead to permanent neurological consequences [see Warnings and Precautions (5.8)].

Respiratory Effects

Advise patients that they should contact their healthcare provider if they experience new onset or worsening dyspnea [see Warnings and Precautions (5.9)].

Immune System Effects after Stopping VELSIPITY

Advise patients that VELSIPITY continues to have effects, such as lowering effects on peripheral lymphocyte count, for up to 5 weeks after the last dose, and to monitor for signs and symptoms of infection during that time [see Warnings and Precautions (5.11)].

This product’s labeling may have been updated. For the most recent prescribing information, please visit www.pfizer.com.

For Medical Information about VELSIPITY, please visit www.pfizermedinfo.com or call 1-800-438-1985.

LAB-1528-4.0

MEDICATION GUIDE
VELSIPITY™ (Vel-sip-itee)
(etrasimod)
tablets, for oral use

Read this Medication Guide before you start taking VELSIPITY and each time you get a refill. There may be new information. This Medication Guide does not take the place of talking with your healthcare provider about your medical condition or treatment.

What is the most important information I should know about VELSIPITY?
VELSIPITY can cause serious side effects, including:

1. Infections. VELSIPITY can increase your risk of serious infections. These infections can be life-threatening and cause death.
  VELSIPITY lowers the number of white blood cells (lymphocytes) in your blood. This usually returns to normal within 4 to 5 weeks after you stop taking VELSIPITY. Your healthcare provider will test your blood before you start taking VELSIPITY. Call your healthcare provider right away if you have any of these symptoms of an infection during treatment with VELSIPITY, and for 5 weeks after you stop taking VELSIPITY:

- fever or high temperature
- tiredness
- flu-like symptoms

- pain when peeing or peeing more often than usual. These can be signs of a urinary tract infection.
- headache with fever, neck stiffness, sensitivity to light, nausea, or confusion. These may be symptoms of meningitis, an infection of the lining around your brain and spine.

Your healthcare provider may delay or stop your VELSIPITY treatment if you have an infection.

2. Slow heart rate (also known as bradyarrhythmia) when you start taking VELSIPITY. VELSIPITY may cause your heart rate to temporarily slow down especially after you take your first dose. You will have a test called an electrocardiogram (ECG) to check the electrical activity of your heart before you take your first dose of VELSIPITY.
  Call your healthcare provider if you experience these symptoms of slow heart rate:

- feeling dizzy
- feeling lightheaded
- feeling like your heart is beating slowly or skipping beats
- feeling short of breath

- feeling confused
- feeling tired
- chest pain

See "What are the possible side effects of VELSIPITY?" for more information about side effects.

What is VELSIPITY?

- VELSIPITY is a prescription medicine used to treat adults with moderately to severely active ulcerative colitis.

It is not known if VELSIPITY is safe and effective in children.

Do not take VELSIPITY if you:

- have had a heart attack, chest pain (unstable angina), stroke or mini stroke (transient ischemic attack or TIA), and certain types of heart failure requiring hospitalization in the last 6 months.
- have or have had a history of unusual heartbeats (arrhythmia) that is not corrected by a pacemaker.

Talk to your healthcare provider before taking VELSIPITY if you have any of these conditions or do not know if you have any of these conditions.

Before taking VELSIPITY, tell your healthcare provider about all of your medical conditions, including if you:

- have a serious infection or an infection that does not go away or that keeps coming back (chronic).
- are unable to fight infections due to a disease.
- have received a vaccine in the past 4 weeks or are scheduled to receive a vaccine. You should be brought up to date with all age required vaccines before starting treatment with VELSIPITY. VELSIPITY may affect how well a vaccine works. Tell your healthcare provider that you are receiving treatment with VELSIPITY before receiving a vaccine.
- have chickenpox or received the vaccine for chickenpox. Your healthcare provider may do a blood test for the chickenpox virus. You may need to get the full course of the chickenpox vaccine and then wait 4 weeks before you start taking VELSIPITY.
- have a slow heart rate.
- have an irregular or abnormal heartbeat (arrhythmia).
- have heart disease, Class I or II heart failure, history of a heart attack, high blood pressure or uncontrolled high blood pressure.
- have cerebrovascular disease or history of a stroke or ministroke.
- history of repeated fainting.
- have or have had liver problems.
- have or have had skin cancer.
- have breathing problems, including untreated sleep apnea.
- are pregnant or plan to become pregnant. VELSIPITY may harm your unborn baby. Talk with your healthcare provider if you are pregnant or plan to become pregnant. If you are a female who can become pregnant, you should use effective birth control during your treatment with VELSIPITY and for 7 days after you stop taking VELSIPITY. Talk to your healthcare provider about what birth control method is right for you during this time. Tell your healthcare provider right away if you become pregnant while taking VELSIPITY or within 7 days after you stop taking VELSIPITY.
  Pregnancy Registry: There is a registry for women who become pregnant during treatment with VELSIPITY. If you become pregnant while taking VELSIPITY, talk to your healthcare provider about registering with the VELSIPITY Pregnancy Registry. The purpose of this registry is to collect information about your health and your baby’s health. Either you or your healthcare provider can contact this registry by calling 1-800-616-3791.
- are breastfeeding or plan to breastfeed. It is not known if VELSIPITY passes into your breast milk. Talk to your healthcare provider about the best way to feed your baby if you take VELSIPITY.

Tell your healthcare provider about all the medicines you take, including prescription and over-the-counter medicines, vitamins, and herbal supplements.
Using VELSIPITY with other medicines can cause serious side effects. Especially tell your healthcare provider if you take or have taken:

- medicines to control your heart rhythm (antiarrhythmics), heartbeat, or blood pressure. These may be called beta blockers or calcium channel blockers.
- medicines that affect your immune system.
- certain medicines known as moderate to strong inhibitors of both CYP2C9 and CYP3A4, medicines such as fluconazole. If you are taking fluconazole, you should not take VELSIPITY.
- Rifampin. If you are taking rifampin, you should not take VELSIPITY.

You should not receive live vaccines at least 4 weeks before starting VELSIPITY, during treatment with VELSIPITY and for 5 weeks after you stop taking VELSIPITY. Talk to your healthcare provider before you receive a vaccine during treatment and for 5 weeks after treatment with VELSIPITY. If you receive a live vaccine, you may get the infection the vaccine was meant to prevent. Vaccines may not work as well when given during treatment with VELSIPITY.
Ask your healthcare provider or pharmacist for a list of these medicines if you are not sure.

Know the medicines you take. Keep a list of your medicines to show the list to your healthcare provider and pharmacist when you get a new medicine.

How should I take VELSIPITY?

- Take VELSIPITY exactly as your healthcare provider tells you to take it.
- Take VELSIPITY 1 time each day.
- Swallow VELSIPITY tablets whole.
- Take VELSIPITY with or without food.
- If a dose is missed, take the missed dose at the next scheduled time; do not double the next dose.

What are the possible side effects of VELSIPITY?
VELSIPITY can cause serious side effects, including:

- See "What is the most important information I should know about VELSIPITY?"
- Liver problems. VELSIPITY may cause liver problems. Your healthcare provider will do blood tests to check your liver before you start taking VELSIPITY. Call your healthcare provider right away if you have any of the following symptoms:

- unexplained nausea
- vomiting
- stomach area (abdominal pain)
- tiredness

- loss of appetite
- yellowing of the whites of your eyes or skin
- dark colored urine

If you develop any of these symptoms, your healthcare provider will do blood tests to check your liver and may stop your treatment with VELSIPITY.
2. Increased blood pressure. Your healthcare provider should check your blood pressure during treatment with VELSIPITY and treat you as needed.
3. A problem with your vision called macular edema. Your healthcare provider should test your vision around the time you start taking VELSIPITY or at any time you notice vision changes during your treatment with VELSIPITY. Call your healthcare provider right away if you have any of the following symptoms:

- blurriness or shadows in the center of your vision
- sensitivity to light

- a blind spot in the center of your vision
- unusually colored vision

- Types of skin cancer. Certain types of skin cancer have happened with medicines in the same class as VELSIPITY. Limit the amount of time you spend in sunlight and ultraviolet (UV) light while taking VELSIPITY. Wear protective clothing and use a sunscreen with a high sun protection factor. Tell your healthcare provider if you have any changes in the appearance of your skin.
- Swelling and narrowing of the blood vessels in your brain. A condition called Posterior Reversible Encephalopathy Syndrome (PRES) has happened with drugs in the same class. Symptoms of PRES usually get better when you discontinue treatment. If not treated, PRES may cause a stroke. Call your healthcare provider right away if you have any of the following symptoms:
  - sudden severe headache
  - sudden confusion
  - sudden loss of vision or other changes in your vision
  - seizure
  - If you develop any of these symptoms, your healthcare provider will stop treatment with VELSIPITY.
- Breathing problems. Some people who take medicines in the same class as VELSIPITY may experience shortness of breath. Your healthcare provider may do tests to check your breathing during treatment with VELSIPITY. Call your healthcare provider right away if you have new or worsening breathing problems.

The most common side effects of VELSIPITY include headache, elevated liver tests, and dizziness.
Tell your healthcare provider if you have any side effect that bothers you or that does not go away. These are not all of the possible side effects of VELSIPITY.
For more information, ask your healthcare provider or pharmacist. Call your doctor for medical advice about side effects. You may report side effects to FDA at 1-800-FDA-1088.
You may also report side effects to Pfizer at 1-800-438-1985.

How should I store VELSIPITY?

- Store VELSIPITY at room temperature between 68°F to 77°F (20°C to 25°C).

Keep VELSIPITY and all medicines out of the reach of children.

General information about the safe and effective use of VELSIPITY.
Medicines are sometimes prescribed for purposes other than those listed in a Medication Guide. Do not use VELSIPITY for a condition for which it was not prescribed. Do not give VELSIPITY to other people, even if they have the same symptoms you have. It may harm them. You can ask your pharmacist or healthcare provider for information about VELSIPITY that is written for health professionals.

What are the ingredients in VELSIPITY?
Active ingredient: etrasimod arginine.
Inactive ingredients:
Tablet core: magnesium stearate, mannitol, microcrystalline cellulose, and sodium starch glycolate.
Tablet coating: FD&C blue #1/brilliant blue FCF aluminum lake, FD&C blue #2/indigo carmine aluminum lake, FD&C yellow #5/tartrazine aluminum lake, macrogol 4000 JP/PEG 3350, polyvinyl alcohol (partially hydrolyzed), talc, and titanium dioxide.

LAB-1541-2.0

This Medication Guide has been approved by the U.S. Food and Drug Administration. Revised: 06/2024

PRINCIPAL DISPLAY PANEL - 2 mg Tablet Blister Label

ALWAYS DISPENSE WITH MEDICATION GUIDE
PROFESSIONAL SAMPLE–NOT FOR SALE

NDC 63539-274-28

Pfizer

Velsipity™
(etrasimod) tablets

2 mg

Recommended Dosage: See
Prescribing Information

28 Tablets
Rx only

PRINCIPAL DISPLAY PANEL - 2 mg Tablet Bottle Label

ALWAYS DISPENSE WITH MEDICATION GUIDE
PROFESSIONAL SAMPLE–NOT FOR SALE

NDC 63539-274-30

Pfizer

Velsipity®
(etrasimod) tablets

2 mg

30 Tablets
Rx only

Store at 20ºC to 25ºC (68ºF to

77ºF); excursions permitted

between 15ºC to 30ºC (59ºF

to 86ºF) [see USP Controlled

Room Temperature].

Keep out of reach of children.

Recommended Dosage: See

Prescribing Information.

Each tablet contains:
Etrasimod…2 mg
(equivalent to 2.76 mg
etrasimod arginine)

Distributed by
U.S. Pharmaceuticals
Pfizer Inc.
New York, NY 10001

PRINCIPAL DISPLAY PANEL - 2 mg Tablet Carton Label

ALWAYS DISPENSE WITH
MEDICATION GUIDE
PROFESSIONAL SAMPLE–NOT FOR SALE

NDC 63539-274-30

Pfizer

Velsipity®
(etrasimod) tablets

2 mg

30 Tablets
Rx only